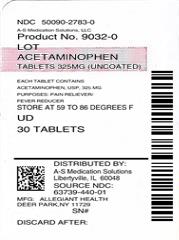 DRUG LABEL: Acetaminophen
NDC: 50090-2783 | Form: TABLET
Manufacturer: A-S Medication Solutions
Category: otc | Type: HUMAN OTC DRUG LABEL
Date: 20210301

ACTIVE INGREDIENTS: ACETAMINOPHEN 325 mg/1 1
INACTIVE INGREDIENTS: STARCH, CORN

Acetaminophen Tablets, 325mg (uncoated)

Active Ingredient (in each tablet)/Purpose

Acetaminophen 325mg....................Analgesic/Antipyretic

Uses

temporary relief of minor aches and pains associated with

- common cold
- headache
- toothache
- muscular aches
- backache
- arthritis
- menstrual cramps
- and reduction of fever

Purpose

Analgesic/Antipyretic

Warnings

Alcohol warning:

If you consume 3 or more alcoholic drinks every day, ask
your doctor whether you should take acetaminophen or other pain relievers/fever
reducers. Acetaminophen may cause liver damage.

Do not use

with any other products containing acetaminophen.

Stop use and ask a doctor if

- symptoms do not improve
- pain gets worse or lasts for more than 10 days
- fever gets worse or lasts for more than 3 days
- new symptoms occur
- redness or swelling is present
- a rare sensitivity reaction occurs

If pregnant or breast-feeding

ask a health professional before use.

Keep out of reach of children.

In case of accidental overdose, contact a doctor or Poison Control Center immediately. Prompt medical attention is critical for adults as well as for children even if you do not notice any signs or symptoms. Do not exceed recommended dosage.

Directions

Adults and children 12 years of age and older

- take 2 tablets every 4 to 6 hours as needed. Do not take more than 12 tablets in 24 hours.

Children 6-11 years of age

- Take 1 tablet every 4 to 6 hours as needed. Do not take more than 5 tablets in 24 hours.

Children under 6 years of age

- Do not use this regular strength product. This will provide more than the recommended dose (overdose) and could cause serious health problems.

Other Information

- store at room temperature 59°-86°F (15°-30°C).

Inactive Ingredients corn starch, pregelatinized starch, stearic acid.

May contain povidone and sodium starch glycolates.

HOW SUPPLIED

Product: 50090-2783

NDC: 50090-2783-0 1 TABLET in a BLISTER PACK / 30 in a BOX, UNIT-DOSE

NDC: 50090-2783-1 30 TABLET in a BLISTER PACK / 25 in a BOX, UNIT-DOSE